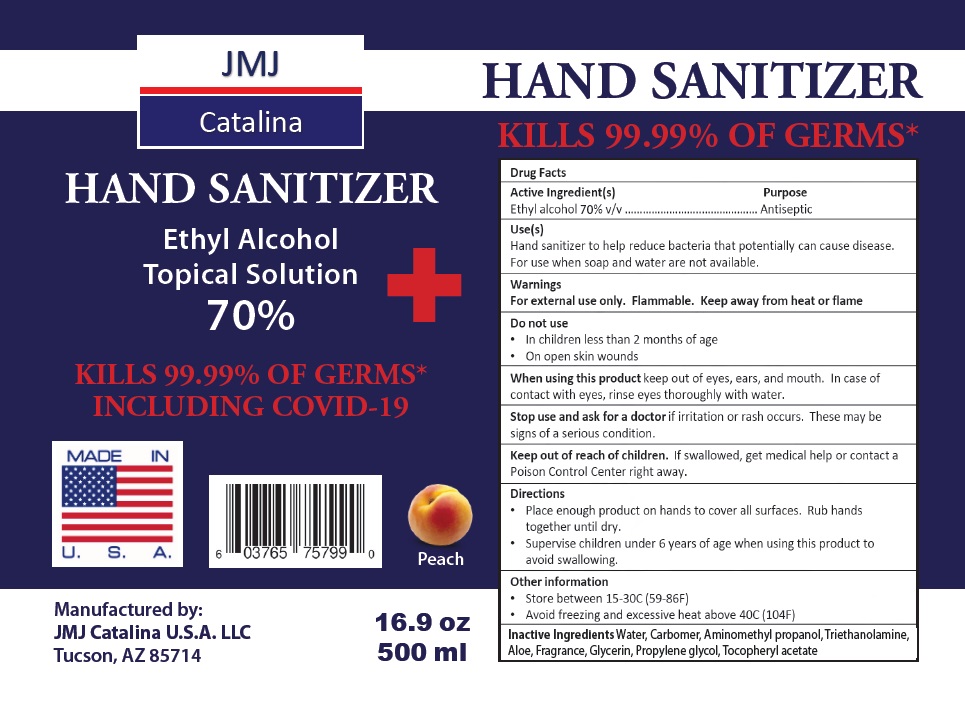 DRUG LABEL: JMJ Catalina
NDC: 78938-333 | Form: GEL
Manufacturer: JMJ CATALINA USA LLC
Category: otc | Type: HUMAN OTC DRUG LABEL
Date: 20200616

ACTIVE INGREDIENTS: ALCOHOL 70 mL/100 mL
INACTIVE INGREDIENTS: WATER; CARBOMER HOMOPOLYMER, UNSPECIFIED TYPE; AMINOMETHYLPROPANOL; TROLAMINE; ALOE; GLYCERIN; PROPYLENE GLYCOL; .ALPHA.-TOCOPHEROL ACETATE

JMJ Catalina HAND SANITIZER

Active Ingredient(s)

Ethyl alcohol 70% v/v

Purpose

Antiseptic

Use(s)

Hand sanitizer to help reduce bacteria that potentially can cause disease.

For use when soap and water are not available.

Warnings

For external use only. Flammable. Keep away from heat or flame

Do not use

• In children less than 2 months of age

• On open skin wounds

When using this product keep out of eyes, ears, and mouth. In case of contact with eyes, rinse eyes thoroughly with water.

Stop use and ask for a doctor if irritation or rash occurs. These may be signs of a serious condition.

Keep out of reach of children. If swallowed, get medical help or contact a Poison Control Center right away.

Directions

• Place enough product on hands to cover all surfaces. Rub hands together until dry.

• Supervise children under 6 years of age when using this product to avoid swallowing.

Other information

• Store between 15-30C (59-86F)

• Avoid freezing and excessive heat above 40C (104F)

INACTIVE INGREDIENT

Inactive Ingredients Water, Carbomer, Aminomethyl propanol, Triethanolamine, Aloe, Fragrance, Glycerin, Propylene glycol, Tocopheryl acetate

Topical Solution

KILLS 99.99% OF GERMS* INCLUDING COVID-19

MADE IN U. S. A.

Peach

Manufactured by:

JMJ Catalina U. S. A. LLC

Tucson, AZ 85714